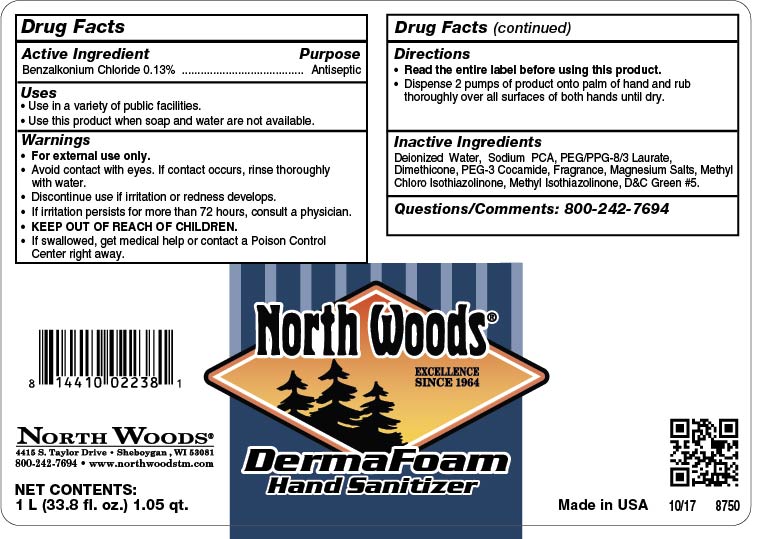 DRUG LABEL: North Woods Derma Foam Hand Sanitizer
NDC: 53125-700 | Form: SOAP
Manufacturer: Superior Chemical Corporation
Category: otc | Type: HUMAN OTC DRUG LABEL
Date: 20190409

ACTIVE INGREDIENTS: BENZALKONIUM CHLORIDE 1.3 mg/1 mL
INACTIVE INGREDIENTS: WATER; SODIUM PYRROLIDONE CARBOXYLATE; POLYETHYLENE GLYCOL 400; DIMETHICONE; DMDM HYDANTOIN; PEG-3 COCAMINE; IODOPROPYNYL BUTYLCARBAMATE; D&C GREEN NO. 5

North Woods Derma Foam Hand Sanitizer

Active Ingredient

Benzalkonium Chloride 0.13%

Uses

- Use in a variety of public facilities.
- Use this product when soap and water are not available.

Warnings

- For external use only.
- Avoid contact with eyes.
- Children under the age of 6 should be supervised by an adult when using this product.
- Discontinue use is irritation or redness develops.
- If irritation persists for more than 72 hours, consult a physician.
- KEEP OUT OF REACH OF CHILDREN.

Directions

- Read the entire label before using this product.
- Dispense product onto dry hands. Rub hands together until hands are dry.
- Use as needed between hand washes to reduce bacteria on the skin.

Inactive Ingredients

Deionized Water, Sodium PCA, PEG/PPG-8/3 Laurate, Dimethicone, DMDM Hydantoin, PEG-3 Cocamide, Fragrance, Iodoproynyl Btylcarbamate, D&C Green #5.

Questions or Comments? Phone: (800) 777-9343

MDS information:(800) 891-4965

Purpose

Antiseptic

KEEP OUT OF REACH OF CHILDREN

Superior Derma Foam Hand Sanitizer

75229-00_Superior Derma Foam Hand Sanitizer.